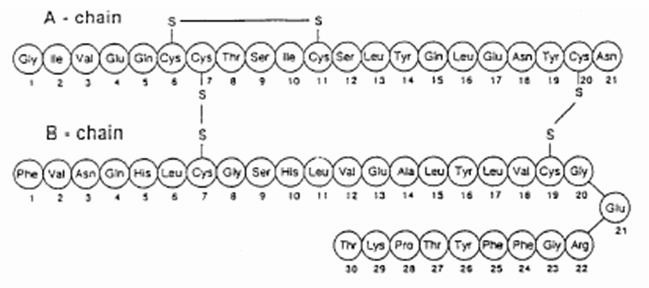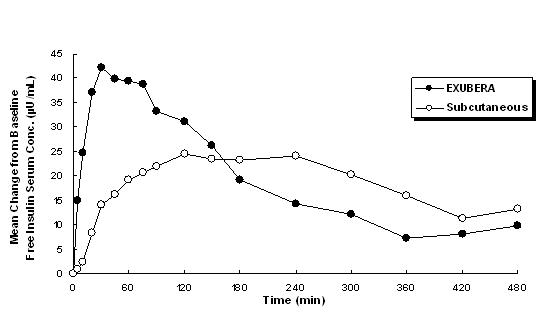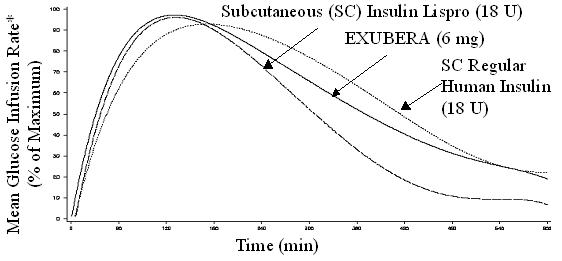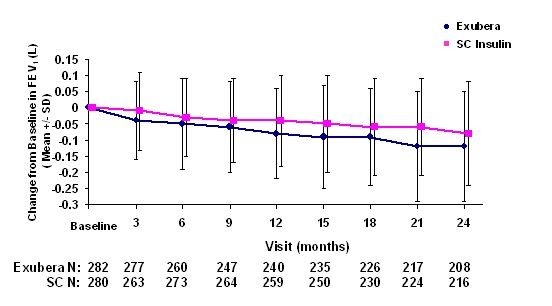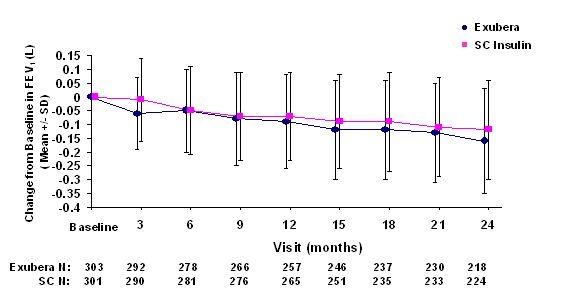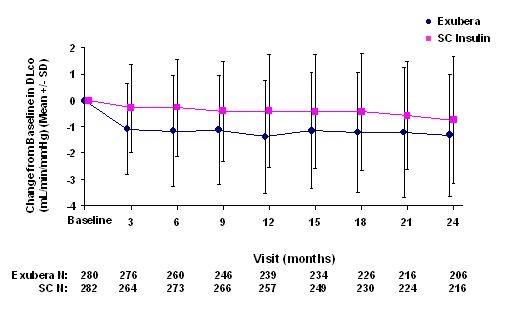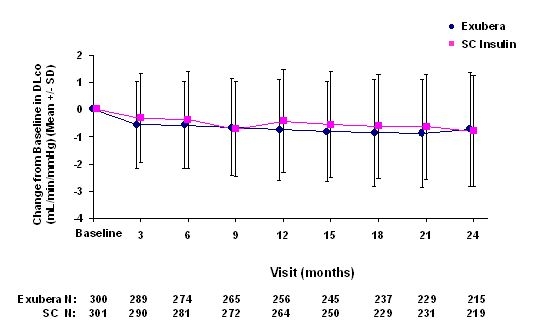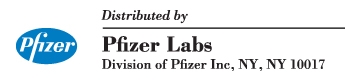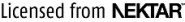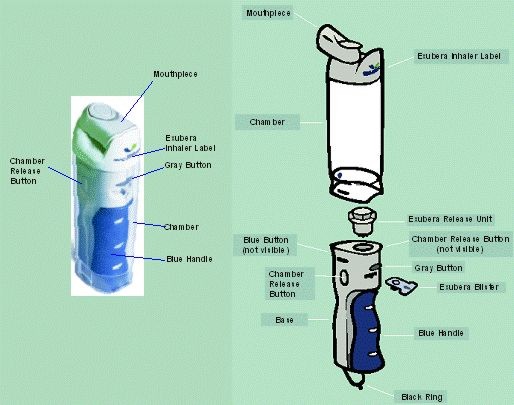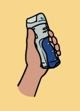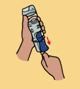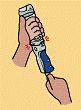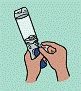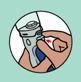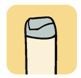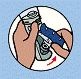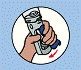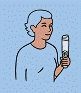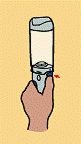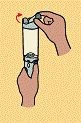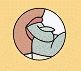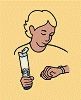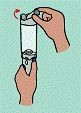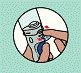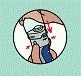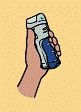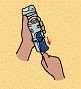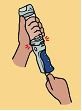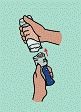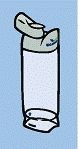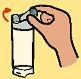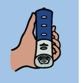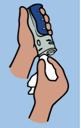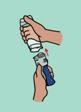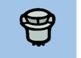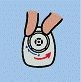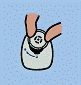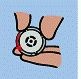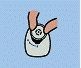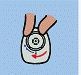 DRUG LABEL: Unknown
Manufacturer: Pfizer Inc.
Category: prescription | Type: HUMAN PRESCRIPTION DRUG LABEL
Date: 20080408

EXUBERA®
(insulin human [rDNA origin]) Inhalation Powder
EXUBERA® Inhaler

Rx only

DESCRIPTION

EXUBERA® consists of blisters containing human insulin inhalation powder, which are administered using the EXUBERA® Inhaler. EXUBERA blisters contain human insulin produced by recombinant DNA technology utilizing a non-pathogenic laboratory strain of Escherichia coli (K12). Chemically, human insulin has the empirical formula C257H383N65O77S6 and a molecular weight of 5808. Human insulin has the following primary amino acid sequence:

EXUBERA (insulin human [rDNA origin]) Inhalation Powder is a white to off-white powder in a unit dose blister (fill mass, see Table 1). Each unit dose blister of EXUBERA contains a 1 mg or 3 mg dose of insulin (see Table 1) in a homogeneous powder formulation containing sodium citrate (dihydrate), mannitol, glycine, and sodium hydroxide. After an EXUBERA blister is inserted into the inhaler, the patient pumps the handle of the inhaler and then presses a button, causing the blister to be pierced. The insulin inhalation powder is then dispersed into the chamber, allowing the patient to inhale the aerosolized powder.

Under standardized in vitro test conditions, EXUBERA delivers a specific emitted dose of insulin from the mouthpiece of the inhaler (see Table 1). A fraction of the total particle mass is emitted as fine particles capable of reaching the deep lung. Up to 45% of the 1 mg blister contents, and up to 25% of the 3 mg blister contents, may be retained in the blister.

Table 1: Dose Nomenclature and Information
Fill Mass (mg powder) | Nominal Dose (mg insulin) | Emitted Dose [Flow rate of 30 L/min for 2.5 seconds] , [Emitted dose and fine particle dose information are not intended to predict actual pharmacodynamic response.] (mg insulin) | Fine Particle Dose [Flow rate of 28.3 L/min for 3 seconds] , (mg insulin)
1.7 | 1.0 | 0.53 | 0.4
5.1 | 3.0 | 2.03 | 1.0

The actual amount of insulin delivered to the lung will depend on individual patient factors, such as inspiratory flow profile. In vitro, emitted aerosol metrics are unaffected at flow rates above 10 L/min.

CLINICAL PHARMACOLOGY

Mechanism of Action

The primary activity of insulin is regulation of glucose metabolism. Insulin lowers blood glucose concentrations by stimulating peripheral glucose uptake by skeletal muscle and fat, and by inhibiting hepatic glucose production. Insulin inhibits lipolysis in the adipocyte, inhibits proteolysis, and enhances protein synthesis.

Pharmacokinetics

Absorption

EXUBERA delivers insulin by oral inhalation. The insulin is absorbed as quickly as subcutaneously administered rapid-acting insulin analogs and more quickly than subcutaneously administered regular human insulin in healthy subjects and in patients with type 1 or type 2 diabetes (see Figure 1).

Figure 1: Mean Changes in Free Insulin Serum Concentrations (µU/mL) in Patients with Type 2 Diabetes Following Administration of Single Doses of Inhaled Insulin from EXUBERA (6 mg) and Subcutaneous Regular Human Insulin (18U)

In clinical studies in patients with type 1 and type 2 diabetes, after inhalation of EXUBERA, serum insulin reached peak concentration more quickly than after subcutaneous injection of regular human insulin, 49 minutes (range 30 to 90 minutes) compared to 105 minutes (range 60 to 240 minutes), respectively.

In clinical studies, the absorption of subcutaneous regular human insulin declined with increasing patient body mass index (BMI). However, the absorption of insulin following inhalation of EXUBERA was independent of BMI.

In a study in healthy subjects, systemic insulin exposure (AUC and Cmax) following administration of EXUBERA increased with dose over a range of 1 to 6 mg when administered as combinations of 1 and 3 mg blisters.

In a study where the dosage form of three 1 mg blisters was compared with one 3 mg blister, Cmax and AUC after administration of three 1 mg blisters were approximately 30% and 40% greater, respectively, than that after administration of one 3 mg blister (see DOSAGE AND ADMINISTRATION).

Distribution and Elimination

Because recombinant human insulin is identical to endogenous insulin, the systemic distribution and elimination are expected to be the same. However, this has not been confirmed for EXUBERA.

Pharmacodynamics

EXUBERA, like subcutaneously administered rapid-acting insulin analogs, has a more rapid onset of glucose-lowering activity than subcutaneously administered regular human insulin. In healthy volunteers, the duration of glucose-lowering activity for EXUBERA was comparable to subcutaneously administered regular human insulin and longer than subcutaneously administered rapid-acting insulin analogs (see Figure 2).

Figure 2. Mean Glucose Infusion Rate (GIR) Normalized to GIRmax for Each Subject Treatment Versus Time in Healthy Volunteers

*Determined as amount of glucose infused to maintain constant plasma glucose concentrations, normalized to maximum values (percent of maximum values); indicative of insulin activity.

When EXUBERA is inhaled, the onset of glucose-lowering activity in healthy volunteers occurs within 10–20 minutes. The maximum effect on glucose lowering is exerted approximately 2 hours after inhalation. The duration of glucose-lowering activity is approximately 6 hours.

In patients with type 1 or type 2 diabetes, EXUBERA has a greater glucose-lowering effect within the first two hours after dosing when compared with subcutaneously administered regular human insulin.

The intra-subject variability of glucose-lowering activity of EXUBERA is generally comparable to that of subcutaneously administered regular human insulin in patients with type 1 and 2 diabetes.

Special Populations

Pediatric Patients

In children (6–11 years) and adolescents (12–17 years) with type 1 diabetes, time to peak insulin concentration for EXUBERA was achieved faster than for subcutaneous regular human insulin, which is consistent with observations in adult patients with type 1 diabetes.

Geriatric Patients

There are no apparent differences in the pharmacokinetic properties of EXUBERA when comparing patients over the age of 65 years and younger adult patients.

Gender

In subjects with and without diabetes, no apparent differences in the pharmacokinetic properties of EXUBERA were observed between men and women.

Race

A study was performed in 25 healthy Caucasian and Japanese non-diabetic subjects to compare the pharmacokinetic and pharmacodynamic properties of EXUBERA, versus subcutaneous injection of regular human insulin. The pharmacokinetic and pharmacodynamic properties of EXUBERA were comparable between the two populations.

Obesity

The absorption of EXUBERA is independent of patient BMI.

Renal Impairment

The effect of renal impairment on the pharmacokinetics of EXUBERA has not been studied. Careful glucose monitoring and dose adjustments of insulin may be necessary in patients with renal dysfunction (see PRECAUTIONS, Renal Impairment).

Hepatic Impairment

The effect of hepatic impairment on the pharmacokinetics of EXUBERA has not been studied. Careful glucose monitoring and dose adjustments of insulin may be necessary in patients with hepatic dysfunction (see PRECAUTIONS, Hepatic Impairment).

Pregnancy

The absorption of EXUBERA in pregnant patients with gestational and pre-gestational type 2 diabetes was consistent with that in non-pregnant patients with type 2 diabetes (see PRECAUTIONS, Pregnancy).

Smoking

In smokers, the systemic insulin exposure for EXUBERA is expected to be 2 to 5 fold higher than in non-smokers. EXUBERA is contraindicated in patients who smoke or who have discontinued smoking less than 6 months prior to starting EXUBERA therapy. If a patient starts or resumes smoking, EXUBERA must be discontinued immediately due to the increased risk of hypoglycemia, and an alternative treatment must be utilized (see CONTRAINDICATIONS).

In clinical studies of EXUBERA in 123 patients (69 of whom were smokers), smokers experienced a more rapid onset of glucose-lowering action, greater maximum effect, and a greater total glucose-lowering effect (particularly during the first 2–3 hours after dosing), compared to non-smokers.

Passive Cigarette Smoke

In contrast to the increase in insulin exposure following active smoking, when EXUBERA was administered to 30 healthy non-smoking volunteers following 2 hours of exposure to passive cigarette smoke in a controlled experimental setting, insulin AUC and Cmax were reduced by approximately 20% and 30%, respectively. The pharmacokinetics of EXUBERA have not been studied in nonsmokers who are chronically exposed to passive cigarette smoke.

Patients with Underlying Lung Diseases

The use of EXUBERA in patients with underlying lung disease, such as asthma or COPD, is not recommended because the safety and efficacy of EXUBERA in this population have not been established (see WARNINGS). The use of EXUBERA is contraindicated in patients with unstable or poorly controlled lung disease, because of wide variations in lung function that could affect the absorption of EXUBERA and increase the risk of hypoglycemia or hyperglycemia (see CONTRAINDICATIONS).

In a pharmacokinetic study in 24 non-diabetic subjects with mild asthma, the absorption of insulin following administration of EXUBERA, in the absence of treatment with a bronchodilator, was approximately 20% lower than the absorption seen in subjects without asthma. However, in a study in 24 non-diabetic subjects with Chronic Obstructive Pulmonary Disease (COPD), the systemic exposure following administration of EXUBERA was approximately two-fold higher than that in normal subjects without COPD (see PRECAUTIONS, Underlying Lung Disease).

Administration of albuterol 30 minutes prior to administration of EXUBERA in non-diabetic subjects with both mild asthma (n=36) and moderate asthma (n=31) resulted in a mean increase in insulin AUC and Cmax of between 25 and 50% compared to when EXUBERA was administered alone (see PRECAUTIONS, Drug Interactions).

CLINICAL STUDIES

The safety and efficacy of EXUBERA has been studied in approximately 2500 adult patients with type 1 and type 2 diabetes. The primary efficacy parameter for most studies was glycemic control, as measured by the reduction from baseline in hemoglobin A1c (HbA1c).

Type 1 Diabetes

A 24-week, randomized, open-label, active-control study (Study A) was conducted in patients with type 1 diabetes to assess the safety and efficacy of EXUBERA administered pre-meal three times daily (TID) with a single nighttime injection of Humulin® U Ultralente® (human insulin extended zinc suspension) (n = 136). The comparator treatment was subcutaneous regular human insulin administered twice daily (BID) (pre-breakfast and pre-dinner) with BID injection of NPH human insulin (human insulin isophane suspension) (n = 132). In this study, the mean age was 38.2 years (range: 20–64) and 52% of the subjects were male.

A second 24-week, randomized, open-label, active-control study (Study B) was conducted in patients with type 1 diabetes to assess the safety and efficacy of EXUBERA (n = 103) compared to subcutaneous regular human insulin (n = 103) when administered TID prior to meals. In both treatment arms, NPH human insulin was administered BID (in the morning and at bedtime) as the basal insulin. In this study, the mean age was 38.4 years (range: 19–65) and 54% of the subjects were male.

In each study, the reduction in HbA1c and the rates of hypoglycemia were comparable for the two treatment groups. EXUBERA-treated patients had a greater reduction in fasting plasma glucose than patients in the comparator group. The percentage of patients reaching an HbA1c level of <8% (per American Diabetes Association treatment Action Level at the time of study conduct) and an HbA1c level of <7% was comparable between the two treatment groups. The results for Studies A and B are shown in Table 2.

Table 2: Results of Two 24-Week, Active-Control, Open-Label Trials in Patients With Type 1 Diabetes (Studies A and B)
 | Study A |  | Study B
 | EXUBERA (TID) + UL (QD) | SC R (BID) + NPH (BID) | EXUBERA (TID) + NPH (BID) | SC R (TID) + NPH (BID)
Sample Size | 136 | 132 | 103 | 103
HbA1c (%)
Baseline mean | 7.9 | 8.0 | 7.8 | 7.8
Adj. mean change from baseline | -0.2 | -0.4 | -0.3 | -0.2
EXUBERA minus SC R [A negative treatment difference favors EXUBERA] | 0.14 |  | -0.11
95% CI for treatment difference | (-0.03, 0.32) |  | (-0.30, 0.08)
Fasting Plasma Glucose (mg/dL)
Baseline mean | 191 | 198 | 178 | 191
Adj. mean change from baseline | -32 | -6 | -23 | 13
EXUBERA minus SC R | -27 |  | -35
95% CI for treatment difference | (-47, -6) |  | (-58, -13)
2-hr Post-Prandial Glucose Concentration (mg/dL)
Baseline mean | 283 | 305 | 273 | 293
Adj. mean change from baseline | -21 | 14 | -1 | -3
EXUBERA minus SC R | -35 |  | 2
95% CI for treatment difference | (-61, -8) |  | (-29, 32)
Patients with end-of-study HbA1c < 8% [American Diabetes Association treatment Action Level at the time of study conduct] | 64.0% | 68.2% | 74.8% | 66.0%
Patients with end-of-study HbA1c < 7% | 16.9% | 19.7% | 28.2% | 30.1%
Body Weight
Baseline mean (kg) | 77.4 | 76.4 | 76.0 | 76.9
Adj. mean change from baseline (kg) | 0.4 | 1.1 | 0.4 | 0.6
EXUBERA minus SC R | -0.72 |  | -0.24
95% CI for treatment difference | (-1.48, 0.04) |  | (-1.07, 0.59)
End of study daily insulin dose
Short-acting insulin | 13.4 mg [1 mg inhaled insulin from Exubera is approximately equivalent to 3 IU of subcutaneously injected regular human insulin (See DOSAGE AND ADMINISTRATION)] | 18.3 IU | 10.9 mg | 25.7 IU
Long-acting insulin | 26.4 IU | 37.1 IU | 31.5 IU | 31.9 IU
UL = Humulin® U Ultralente®; SC R = subcutaneous regular human insulin

Type 2 Diabetes

Monotherapy in Patients Not Optimally Controlled With Diet and Exercise Treatment

A 12-week, randomized, open-label, active-control study (Study C) was conducted in patients with type 2 diabetes not optimally controlled with diet and exercise, assessing the safety and efficacy of pre-meal TID EXUBERA (n = 75) compared to an insulin-sensitizing agent. In this study, the mean age was 53.7 years (range: 28–80), 55% of the subjects were male and the mean body mass index was 32.3 kg/m^2.

At 12 weeks, HbA1c levels in patients treated with EXUBERA decreased 2.2% (SD = 1.0) from a baseline of 9.5% (SD = 1.1). The proportion of patients treated with EXUBERA reaching an end-of-study HbA1c level of <8% increased to 82.7%. The proportion of patients treated with EXUBERA reaching an end-of-study HbA1c level of <7 % was 44.6%. Fasting plasma glucose levels in patients treated with EXUBERA decreased 60 mg/dl from a baseline of 208 mg/dl. Patients treated with EXUBERA experienced a mean increase in body weight of 2 kg. The rate of hypoglycemia was higher in the Exubera group than the group receiving an insulin-sensitizing agent.

Monotherapy and Add-On Therapy in Patients Previously Treated With Oral Agent Therapy

A 12-week, randomized, open-label, active-control study (Study D) was conducted in patients with type 2 diabetes who were currently receiving treatment, but were poorly controlled, with two oral agents (OA). Baseline OAs included an insulin secretagogue, and either metformin or a thiazolidinedione. Patients were randomized to one of three arms: continuing OA therapy alone (n = 96), switching to pre-meal TID EXUBERA monotherapy (n = 102) or adding pre-meal TID EXUBERA to continued OA therapy (n = 100). In this study, the mean age was 57.4 years (range: 33–80), 66% of the subjects were male and the mean body mass index was 30 kg/m^2.

EXUBERA monotherapy and EXUBERA in combination with OA therapy were superior to OA therapy alone in reducing HbA1c levels from baseline. The rates of hypoglycemia for the two EXUBERA treatment groups were slightly higher than in the OA therapy alone group. Compared to OA therapy alone, the percentage of patients reaching an HbA1c level of <8% (per American Diabetes Association treatment Action Level at time of study conduct) and an HbA1c level of <7% was greater for patients treated with EXUBERA monotherapy and EXUBERA in combination with OA therapy. Patients in both EXUBERA treatment groups had greater reductions in fasting plasma glucose than patients treated with OA therapy alone. The results for Study D are shown in Table 3.

Table 3: Results of a 12-Week, Active-Control, Open-Label Trial in Patients With Type 2 Diabetes Not Optimally Controlled With Dual Oral Agent Therapy (Study D)
Study D | EXUBERA monotherapy |  | OAs [OAs = treatment with two oral agents (an insulin secretagogue in addition to metformin or a thiazolidinedione)] |  | EXUBERA + OAs
Sample Size | 102 |  | 96 |  | 100
HbA1c (%)
Baseline mean | 9.3 |  | 9.3 |  | 9.2
Adj. mean change from baseline | -1.4 |  | -0.2 |  | -1.9
EXUBERA group minus OAs [A negative treatment difference favors EXUBERA] | -1.18, [Comparison of EXUBERA monotherapy to combination oral agent therapy alone] , [p < 0.0001] |  |  | -1.67, [Comparison of EXUBERA plus oral agents to combination oral agent therapy alone] ,
95% CI for treatment difference | (-1.41, -0.95) |  |  | (-1.90, -1.44)
Fasting Plasma Glucose (mg/dL)
Baseline mean | 203 |  | 203 |  | 195
Adj. mean change from baseline | -23 |  | 1 |  | -53
EXUBERA group minus OAs | -24 |  |  | -53
95% CI for treatment difference | (-36, -11) |  |  | (-66, -41)
Patients with end-of-study HbA1c < 8% [American Diabetes Association treatment Action Level at the time of study conduct] | 55.9% |  | 18.8% |  | 86.0%
Patients with end-of-study HbA1c < 7% | 16.7% |  | 1.0% |  | 32.0%
Body Weight
Baseline mean (kg) | 89.5 |  | 88.0 |  | 88.6
Adj. mean change from baseline (kg) | 2.8 |  | 0.0 |  | 2.7
EXUBERA group minus OAs | 2.80 |  |  | 2.75
95% CI for treatment difference | (1.94, 3.65) |  |  | (1.89, 3.61)

A 24-week, randomized, open-label, active-control study (Study E) was conducted in patients with type 2 diabetes, currently receiving sulfonylurea therapy. This study was designed to assess the safety and efficacy of the addition of pre-meal EXUBERA to continued sulfonylurea therapy (n = 214) compared to the addition of pre-meal metformin to continued sulfonylurea therapy (n = 196). Subjects were stratified according to their HbA1c at Week -1. Two strata were defined: a low HbA1c stratum (HbA1c ≥8% to ≤9.5%) and a high HbA1c stratum (HbA1c >9.5 to ≤12%).

EXUBERA in combination with sulfonylurea was superior to metformin and sulfonylurea in reducing HbA1c values from baseline in the high stratum group. EXUBERA in combination with sulfonylurea was comparable to metformin in combination with sulfonylurea in reducing HbA1c values from baseline in the low stratum group. The rate of hypoglycemia was higher after the addition of EXUBERA to sulfonylurea than after the addition of metformin to sulfonylurea. The percentage of patients reaching target HbA1c values of 8% and 7% was comparable between treatment groups in both strata, as was reduction in fasting plasma glucose (see Table 4).

Another 24-week, randomized, open-label, active-control study (Study F) was conducted in patients with type 2 diabetes, currently receiving metformin therapy. This study was designed to assess the safety and efficacy of the addition of pre-meal EXUBERA to continued metformin therapy (n = 234) compared to the addition of pre-meal glibenclamide to continued metformin therapy (n = 222). Subjects in this study were also stratified to one of two strata as defined in Study E.

EXUBERA in combination with metformin was superior to glibenclamide and metformin in reducing HbA1c values from baseline and achieving target HbA1c values in the high stratum group. EXUBERA in combination with metformin was comparable to glibenclamide in combination with metformin in reducing HbA1c values from baseline and achieving target HbA1c values in the low stratum group. The rate of hypoglycemia was slightly higher after the addition of EXUBERA to metformin than after the addition of glibenclamide to metformin. Reduction in fasting plasma glucose was comparable between treatment groups (see Table 4).

Table 4: Results of Two 24-Week, Active-Control, Open-Label Trials in Patients With Type 2 Diabetes Previously On Oral Agent Therapy (Studies E and F)
 | Study E |  |  |  | Study F
 | Exubera + SU [SU = sulfonylurea, Met = metformin, Gli = glibenclamide] | Met+ SU | Exubera + SU | Met+ SU | Exubera + Met | Gli + Met | Exubera + Met | Gli + Met
 | High stratum [Low stratum = entry HbA1c ≥8.0% to ≤9.5%; high stratum = entry HbA1c >9.5% to ≤12%] |  | Low stratum |  | High stratum |  | Low stratum
Sample Size | 113 | 103 | 101 | 93 | 109 | 103 | 125 | 119
HbA1c (%)
Baseline mean | 10.5 | 10.6 | 8.8 | 8.8 | 10.4 | 10.6 | 8.6 | 8.7
Adj. mean change from baseline | -2.2 | -1.8 | -1.9 | -1.9 | -2.2 | -1.9 | -1.8 | -1.9
EXUBERA minus OA [A negative treatment difference favors EXUBERA] | -0.38, [p = 0.002] |  | -0.07 |  | -0.37, [p = 0.004] |  | 0.04
95% CI for treatment difference | (-0.63, -0.14) |  | (-0.33, 0.19) |  | (-0.62, -0.12) |  | (-0.19, 0.27)
Fasting Plasma Glucose (mg/dL)
Baseline mean | 241 | 237 | 197 | 198 | 223 | 243 | 187 | 196
Mean change from baseline | -46 | -47 | -48 | -52 | -42 | -40 | -46 | -49
EXUBERA minus OA | 1 |  | 4 |  | -2 |  | 4
95% CI for treatment difference | (-11, 12) |  | (-8, 16) |  | (-14, 10) |  | (-7, 15)
Subjects with end-of-study HbA1c < 8% [American Diabetes Association treatment Action Level at the time of study conduct] | 48.7% | 44.7% | 81.2% | 73.1% | 72.5% | 56.3% | 80.8% | 86.6%
Subjects with end-of-study HbA1c < 7% | 20.4% | 14.6% | 30.7% | 32.3% | 33.9% | 17.5% | 40.0% | 42.9%
Body Weight
Baseline mean (kg) | 80.8 | 79.5 | 79.9 | 81.9 | 88.3 | 87.8 | 90.3 | 88.2
Adj. mean change from baseline (kg) | 3.6 | -0.0 | 2.4 | -0.3 | 2.8 | 2.5 | 2.0 | 1.6
EXUBERA minus OA | 3.60 |  | 2.67 |  | 0.26 |  | 0.38
95% CI for treatment difference | (2.81, 4.39) |  | (1.84, 3.51) |  | (-0.70, 1.21) |  | (-0.52, 1.27)

Use in Patients Previously Treated With Subcutaneous Insulin

A 24-week, randomized, open-label, active-control study (Study G) was conducted in insulin-treated patients with type 2 diabetes to assess the safety and efficacy of EXUBERA administered pre-meal TID with a single nighttime injection of Humulin® U Ultralente® (n = 146) compared to subcutaneous regular human insulin administered BID (pre-breakfast and pre-dinner) with BID injection of NPH human insulin (n = 149). In this study, the mean age was 57.5 years (range: 23–80), 66% of the subjects were male and the mean body mass index was 30.3 kg/m^2.

The reductions from baseline in HbA1c, percent of patients reaching an HbA1c level of <8% (per American Diabetes Association treatment Action Level at time of study conduct) and an HbA1c level of <7%, as well as the rates of hypoglycemia, were similar between treatment groups. EXUBERA-treated patients had a greater reduction in fasting plasma glucose than patients in the comparator group. The results for Study G are shown in Table 5.

Table 5: Results of a 24-Week, Active-Control, Open-Label Trial in Patients With Type 2 Diabetes Previously Treated With Subcutaneous Insulin (Study G)
Study G | EXUBERA (TID) + UL (QD) | SC R (BID) + NPH (BID)
Sample Size | 146 | 149
HbA1c (%)
Baseline mean | 8.1 | 8.2
Adj. mean change from baseline | -0.7 | -0.6
EXUBERA minus SC R [A negative treatment difference favors EXUBERA] | -0.07
95% CI for treatment difference | (-0.31, 0.17)
Fasting Plasma Glucose (mg/dL)
Baseline mean | 152 | 159
Adj. mean change from baseline | -22 | -6
EXUBERA minus SC R | -16.36
95% CI for treatment difference | (-27.09, -5.36)
Patients with end-of-study HbA1c < 8% [American Diabetes Association treatment Action Level at the time of study conduct] | 76.0% | 69.1%
Patients with end-of-study HbA1c < 7% | 45.2% | 32.2%
Body Weight
Baseline mean (kg) | 90.6 | 89.0
Adj. mean change from baseline (kg) | 0.1 | 1.3
EXUBERA minus SC R | -1.28
95% CI for treatment difference | (-1.96, -0.60)
End of study daily insulin dose
Short-acting insulin | 16.6 mg [1 mg inhaled insulin from Exubera is approximately equivalent to 3 IU of subcutaneously injected regular human insulin. See DOSAGE AND ADMINISTRATION] | 25.5 IU
Long-acting insulin | 37.9 IU | 52.3 IU
UL = Humulin® U Ultralente®; SC R = subcutaneous regular human insulin

INDICATIONS AND USAGE

EXUBERA is indicated for the treatment of adult patients with diabetes mellitus for the control of hyperglycemia. EXUBERA has an onset of action similar to rapid-acting insulin analogs and has a duration of glucose-lowering activity comparable to subcutaneously administered regular human insulin. In patients with type 1 diabetes, EXUBERA should be used in regimens that include a longer-acting insulin. In patients with type 2 diabetes, EXUBERA can be used as monotherapy or in combination with oral agents or longer-acting insulins.

CONTRAINDICATIONS

EXUBERA is contraindicated in patients hypersensitive to EXUBERA or one of its excipients.

EXUBERA is contraindicated in patients who smoke or who have discontinued smoking less than 6 months prior to starting EXUBERA therapy. If a patient starts or resumes smoking, EXUBERA must be discontinued immediately due to the increased risk of hypoglycemia, and an alternative treatment must be utilized (see CLINICAL PHARMACOLOGY, Special Populations, Smoking). The safety and efficacy of EXUBERA in patients who smoke have not been established.

EXUBERA is contraindicated in patients with unstable or poorly controlled lung disease, because of wide variations in lung function that could affect the absorption of EXUBERA and increase the risk of hypoglycemia or hyperglycemia.

WARNINGS

EXUBERA differs from regular human insulin by its rapid onset of action. When used as mealtime insulin, the dose of EXUBERA should be given within 10 minutes before a meal.

Hypoglycemia is the most commonly reported adverse event of insulin therapy, including EXUBERA. The timing of hypoglycemia may differ among various insulin formulations.

Patients with type 1 diabetes also require a longer-acting insulin to maintain adequate glucose control.

Any change of insulin should be made cautiously and only under medical supervision. Changes in insulin strength, manufacturer, type (e.g., regular, NPH, analogs), or species (animal, human) may result in the need for a change in dosage. Concomitant oral antidiabetic treatment may need to be adjusted.

Glucose monitoring is recommended for all patients with diabetes.

Because of the effect of EXUBERA on pulmonary function, all patients should have pulmonary function assessed prior to initiating therapy with EXUBERA (see PRECAUTIONS: Pulmonary Function).

The use of EXUBERA in patients with underlying lung disease, such as asthma or COPD, is not recommended because the safety and efficacy of EXUBERA in this population have not been established (see PRECAUTIONS: Underlying Lung Disease).

In clinical trials of Exubera, there have been 6 newly diagnosed cases of primary lung malignancies among Exubera-treated patients, and 1 newly diagnosed case among comparator-treated patients. There has also been 1 postmarketing report of a primary lung malignancy in an Exubera-treated patient. In controlled clinical trials of Exubera, the incidence of new primary lung cancer per 100 patient-years of study drug exposure was 0.13 (5 cases over 3900 patient-years) for Exubera-treated patients and 0.02 (1 case over 4100 patient-years) for comparator-treated patients. There were too few cases to determine whether the emergence of these events is related to Exubera. All patients who were diagnosed with lung cancer had a prior history of cigarette smoking.

PRECAUTIONS

General

As with all insulin preparations, the time course of EXUBERA action may vary in different individuals or at different times in the same individual. Adjustment of dosage of any insulin may be necessary if patients change their physical activity or their usual meal plan. Insulin requirements may be altered during intercurrent conditions such as illness, emotional disturbances, or stress.

Hypoglycemia

As with all insulin preparations, hypoglycemic reactions may be associated with the administration of EXUBERA. Rapid changes in serum glucose concentrations may induce symptoms similar to hypoglycemia in persons with diabetes, regardless of the glucose value. Early warning symptoms of hypoglycemia may be different or less pronounced under certain conditions, such as long duration of diabetes, diabetic nerve disease, use of medications such as beta-blockers, or intensified diabetes control (see PRECAUTIONS, Drug Interactions). Such situations may result in severe hypoglycemia (and, possibly, loss of consciousness) prior to patients' awareness of hypoglycemia.

Renal Impairment

Studies have not been performed in patients with renal impairment. As with other insulin preparations, the dose requirements for EXUBERA may be reduced in patients with renal impairment (see CLINICAL PHARMACOLOGY, Special Populations).

Hepatic Impairment

Studies have not been performed in patients with hepatic impairment. As with other insulin preparations, the dose requirements for EXUBERA may be reduced in patients with hepatic impairment (see CLINICAL PHARMACOLOGY, Special Populations).

Allergy

Systemic Allergy

In clinical studies, the overall incidence of allergic reactions in patients treated with EXUBERA was similar to that in patients using subcutaneous regimens with regular human insulin.

As with other insulin preparations, rare, but potentially serious, generalized allergy to insulin may occur, which may cause rash (including pruritus) over the whole body, shortness of breath, wheezing, reduction in blood pressure, rapid pulse, or sweating. Severe cases of generalized allergy, including anaphylactic reactions, may be life threatening. If such reactions occur from EXUBERA, EXUBERA should be stopped and alternative therapies considered.

Antibody Production

Insulin antibodies may develop during treatment with all insulin preparations including EXUBERA. In clinical studies of EXUBERA where the comparator was subcutaneous insulin, increases in insulin antibody levels (as reflected by assays of insulin binding activity) were significantly greater for patients who received EXUBERA than for patients who received subcutaneous insulin only. No clinical consequences of these antibodies were identified over the time period of clinical studies of EXUBERA; however, the long-term clinical significance of this increase in antibody formation is unknown.

Respiratory

Pulmonary Function

In clinical trials up to two years duration, patients treated with EXUBERA demonstrated a greater decline in pulmonary function, specifically the forced expiratory volume in one second (FEV1) and the carbon monoxide diffusing capacity (DLCO), than comparator-treated patients. The mean treatment group difference in pulmonary function favoring the comparator group, was noted within the first several weeks of treatment with EXUBERA, and did not change over the two year treatment period (See ADVERSE REACTIONS: Pulmonary Function).

During the controlled clinical trials, individual patients experienced notable declines in pulmonary function in both treatment groups. A decline from baseline FEV1 of ≥ 20% at last observation occurred in 1.5% of EXUBERA-treated and 1.3% of comparator-treated patients. A decline from baseline DLCO of ≥ 20% at last observation occurred in 5.1% of EXUBERA-treated and 3.6% of comparator treated patients.

Because of the effect of EXUBERA on pulmonary function, all patients should have spirometry (FEV1) assessed prior to initiating therapy with EXUBERA. Assessment of DLCO should be considered. The efficacy and safety of EXUBERA in patients with baseline FEV1 or DLCO < 70% predicted have not been established and the use of EXUBERA in this population is not recommended.

Assessment of pulmonary function (e.g., spirometry) is recommended after the first 6 months of therapy, and annually thereafter, even in the absence of pulmonary symptoms. In patients who have a decline of ≥ 20% in FEV1 from baseline, pulmonary function tests should be repeated. If the ≥ 20% decline from baseline FEV1 is confirmed, EXUBERA should be discontinued. The presence of pulmonary symptoms and lesser declines in pulmonary function may require more frequent monitoring of pulmonary function and consideration of discontinuation of EXUBERA.

Underlying Lung Disease

The use of EXUBERA in patients with underlying lung disease, such as asthma or COPD, is not recommended because the efficacy and safety of EXUBERA in this population have not been established.

Bronchospasm

Bronchospasm has been rarely reported in patients taking EXUBERA. Patients experiencing such a reaction should discontinue EXUBERA and seek medical evaluation immediately. Re-administration of EXUBERA requires a careful risk evaluation, and should only be done under close medical monitoring with appropriate clinical facilities available.

Intercurrent Respiratory Illness

EXUBERA has been administered to patients with intercurrent respiratory illness (e.g. bronchitis, upper respiratory tract infections, rhinitis) during clinical studies. In patients experiencing these conditions, 3–4% temporarily discontinued EXUBERA therapy. There was no increased risk of hypoglycemia or worsened glycemic control observed in EXUBERA-treated patients compared to patients treated with subcutaneous insulin. During intercurrent respiratory illness, close monitoring of blood glucose concentrations, and dose adjustment, may be required.

Information for Patients

Patients should be instructed on self-management procedures including glucose monitoring; proper EXUBERA inhalation technique; and hypoglycemia and hyperglycemia management. Patients must be instructed on handling of special situations such as intercurrent conditions (illness, stress, or emotional disturbances), an inadequate or skipped insulin dose, inadvertent administration of an increased insulin dose, inadequate food intake, or skipped meals. Refer patients to the EXUBERA Patient Medication Guide for additional information.

Patients should be informed that in clinical studies, treatment with EXUBERA was associated with small, non-progressive mean declines in pulmonary function relative to comparator treatments. Because of the effect of EXUBERA on pulmonary function, pulmonary function tests are recommended prior to initiating treatment with EXUBERA. Following initiation of therapy, periodic pulmonary function tests are recommended (see PRECAUTIONS, Respiratory, Pulmonary Function).

Patients should inform their physician if they have a history of lung disease, because the use of EXUBERA is not recommended in patients with underlying lung disease (e.g., asthma or COPD), and is contraindicated in patients with poorly controlled lung disease.

Women with diabetes should be advised to inform their doctor if they are pregnant or are contemplating pregnancy.

Drug Interactions

A number of substances affect glucose metabolism and may require insulin dose adjustment and particularly close monitoring.

The following are examples of substances that may reduce the blood glucose-lowering effect of insulin that may result in hyperglycemia: corticosteroids, danazol, diazoxide, diuretics, sympathomimetic agents (e.g., epinephrine, albuterol, terbutaline), glucagon, isoniazid, phenothiazine derivatives, somatropin, thyroid hormones, estrogens, progestogens (e.g., in oral contraceptives), protease inhibitors, and atypical antipsychotic medications (e.g., olanzapine and clozapine).

The following are examples of substances that may increase the blood glucose-lowering effect of insulin and susceptibility to hypoglycemia: oral antidiabetic products, ACE inhibitors, disopyramide, fibrates, fluoxetine, MAO inhibitors, pentoxifylline, propoxyphene, salicylates, and sulfonamide antibiotics.

Beta-blockers, clonidine, lithium salts, and alcohol may either increase or reduce the blood glucose-lowering effect of insulin. Pentamidine may cause hypoglycemia, which may sometimes be followed by hyperglycemia.

In addition, under the influence of sympatholytic medicinal products such as beta-blockers, clonidine, guanethidine, and reserpine, the signs and symptoms of hypoglycemia may be reduced or absent.

Bronchodilators and other inhaled products may alter the absorption of inhaled human insulin (see CLINICAL PHARMACOLOGY, Special Populations). Consistent timing of dosing of bronchodilators relative to EXUBERA administration, close monitoring of blood glucose concentrations and dose titration as appropriate are recommended.

Carcinogenesis, Mutagenesis, Impairment of Fertility

Two-year carcinogenicity studies in animals have not been performed. Insulin was not mutagenic in the Ames bacterial reverse mutation test in the presence and absence of metabolic activation.

In Sprague-Dawley rats, a 6-month repeat-dose toxicity study was conducted with insulin inhalation powder at doses up to 5.8 mg/kg/day (compared to the clinical starting dose of 0.15 mg/kg/day, the rat high dose was 39 times or 8.3 times the clinical dose, based on either a mg/kg or a mg/m^2 body surface area comparison). In Cynomolgus monkeys, a 6-month repeat-dose toxicity study was conducted with inhaled insulin at doses up to 0.64 mg/kg/day. Compared to the clinical starting dose of 0.15 mg/kg/day, the monkey high dose was 4.3 times or 1.4 times the clinical dose, based on either a mg/kg or a mg/m^2 body surface area comparison. These were maximum tolerated doses based on hypoglycemia.

Compared to control animals, there were no treatment-related adverse effects in either species on pulmonary function, gross or microscopic morphology of the respiratory tract or bronchial lymph nodes. Similarly, there was no effect on cell proliferation indices in alveolar or bronchiolar area of the lung in either species.

Because recombinant human insulin is identical to the endogenous hormone, reproductive/fertility studies were not performed in animals.

Pregnancy

Teratogenic Effects

Pregnancy Category C

Animal reproduction studies have not been conducted with EXUBERA. It is also not known whether EXUBERA can cause fetal harm when administered to a pregnant woman or whether EXUBERA can affect reproductive capacity. EXUBERA should be given to a pregnant woman only if clearly needed.

Nursing Mothers

Many drugs, including human insulin, are excreted in human milk. For this reason, caution should be exercised when EXUBERA is administered to a nursing woman. Patients with diabetes who are lactating may require adjustments in EXUBERA dose, meal plan, or both.

Pediatric Use

Long-term safety and effectiveness of EXUBERA in pediatric patients have not been established (see CLINICAL PHARMACOLOGY, Special Populations).

Geriatric Use

In controlled Phase 2/3 clinical studies (n=1975), EXUBERA was administered to 266 patients ≥65 years of age and 30 patients ≥75 years of age. The majority of these patients had type 2 diabetes. The change in HbA1C and rate of hypoglycemia did not differ by age.

ADVERSE REACTIONS

The safety of EXUBERA alone, or in combination with subcutaneous insulin or oral agents, has been evaluated in approximately 2500 adult patients with type 1 or type 2 diabetes who were exposed to EXUBERA. Approximately 2000 patients were exposed to EXUBERA for greater than 6 months and more than 800 patients were exposed for more than 2 years.

Non-respiratory adverse events reported in ≥1% of 1977 EXUBERA-treated patients in controlled Phase 2/3 clinical studies, regardless of causality, include (but are not limited to) the following:

Metabolic and Nutritional: hypoglycemia (see WARNINGS and PRECAUTIONS)
Body as a whole: chest pain
Digestive: dry mouth
Special senses: otitis media (type 1 pediatric diabetics)

Hypoglycemia

The rates and incidence of hypoglycemia were comparable between EXUBERA and subcutaneous regular human insulin in patients with type 1 and type 2 diabetes. In type 2 patients who were not adequately controlled with single oral agent therapy, the addition of EXUBERA was associated with a higher rate of hypoglycemia than was the addition of a second oral agent.

Chest pain

A range of different chest symptoms were reported as adverse reactions and were grouped under the non-specific term chest pain. These events occurred in 4.7% of EXUBERA-treated patients and 3.2% of patients in comparator groups. The majority (>90%) of these events were reported as mild or moderate. Two patients in the EXUBERA and one in the comparator group discontinued treatment due to chest pain. The incidence of all-causality adverse events related to coronary artery disease, such as angina pectoris or myocardial infarction was comparable in the EXUBERA (0.7% angina pectoris; 0.7% myocardial infarction) and comparator (1.3% angina pectoris; 0.7% myocardial infarction) treatment groups.

Dry Mouth

Dry mouth was reported in 2.4% of EXUBERA-treated patients and 0.8% of patients in comparator groups. Nearly all (>98%) of dry mouth reported was mild or moderate. No patients discontinued treatment due to dry mouth.

Ear Events in Pediatric Diabetics

Pediatric type 1 diabetics in EXUBERA groups experienced adverse events related to the ear more frequently than did pediatric type 1 diabetics in treatment groups receiving only subcutaneous insulin. These events included otitis media (EXUBERA 6.5%; SC 3.4%), ear pain (EXUBERA 3.9%; SC 1.4%), and ear disorder (EXUBERA 1.3%; SC 0%).

Respiratory Adverse Events

Table 6 shows the incidence of respiratory adverse events for each treatment group that were reported in ≥1% of any treatment group in controlled Phase 2 and 3 clinical studies, regardless of causality.

Table 6: Respiratory Adverse Events Reported in ≥1% of Any Treatment Group in Controlled Phase 2 and 3 Clinical Studies, Regardless of Causality
 | Percent of Patients Reporting Event
Adverse Event | Type 1 Diabetes |  | Type 2 Diabetes
Adverse Event | EXUBERA N = 698 | SC N = 705 | EXUBERA N = 1279 | SC N = 488 | OAs N = 644
Respiratory Tract Infection | 43.3 | 42.0 | 29.2 | 38.1 | 19.7
Cough Increased | 29.5 | 8.8 | 21.9 | 10.2 | 3.7
Pharyngitis | 18.2 | 16.6 | 9.5 | 9.6 | 5.9
Rhinitis | 14.5 | 10.9 | 8.8 | 10.5 | 3.0
Sinusitis | 10.3 | 7.4 | 5.4 | 10.0 | 2.3
Respiratory Disorder | 7.4 | 4.1 | 6.1 | 10.2 | 1.7
Dyspnea | 4.4 | 0.9 | 3.6 | 2.5 | 1.4
Sputum Increased | 3.9 | 1.3 | 2.8 | 1.0 | 0.5
Bronchitis | 3.2 | 4.1 | 5.4 | 3.9 | 4.0
Asthma | 1.3 | 1.3 | 2.0 | 2.3 | 0.5
Epistaxis | 1.3 | 0.4 | 1.2 | 0.4 | 0.8
Laryngitis | 1.1 | 0.4 | 0.5 | 0.4 | 0.3
Pneumonia | 0.9 | 1.1 | 0.9 | 1.6 | 0.6
Voice Alteration | 0.1 | 0.1 | 1.3 | 0.0 | 0.3
SC = subcutaneous insulin comparator; OA = oral agent comparators

Cough

In 3 clinical studies, patients who completed a cough questionnaire reported that the cough tended to occur within seconds to minutes after EXUBERA inhalation, was predominantly mild in severity and was rarely productive in nature. The incidence of this cough decreased with continued EXUBERA use. In controlled clinical studies, 1.2% of patients discontinued EXUBERA treatment due to cough.

Dyspnea

Nearly all (>97%) of dyspnea was reported as mild or moderate. A small number of EXUBERA-treated patients (0.4%) discontinued treatment due to dyspnea compared to 0.1% of comparator-treated patients.

Other Respiratory Adverse Events – Pharyngitis, Sputum Increased and Epistaxis

The majority of these events were reported as mild or moderate. A small number of EXUBERA-treated patients discontinued treatment due to pharyngitis (0.2%) and sputum increased (0.1%); no patients discontinued treatment due to epistaxis.

Pulmonary Function

The effect of EXUBERA on the respiratory system has been evaluated in over 3800 patients in controlled phase 2 and 3 clinical studies (in which 1977 patients were treated with EXUBERA). In randomized, open-label clinical trials up to two years duration, patients treated with EXUBERA demonstrated a greater decline in pulmonary function, specifically the forced expiratory volume in one second (FEV1) and the carbon monoxide diffusing capacity (DLCO), than comparator treated patients. The mean treatment group differences in FEV1 and DLCO, were noted within the first several weeks of treatment with EXUBERA, and did not progress over the two year treatment period. In one completed controlled clinical trial in patients with type 2 diabetes following two years of treatment with EXUBERA, patients showed resolution of the treatment group difference in FEV1 six weeks after discontinuation of therapy. Resolution of the effect of EXUBERA on pulmonary function in patients with type 1 diabetes has not been studied after long-term treatment.

Figures 3 through 6 display the mean FEV1 and DLCO change from baseline versus time from two ongoing randomized, open-label, two year studies in 580 patients with type 1 and 620 patients with type 2 diabetes.

Figure 3: Change from Baseline FEV1 (L) in Patients with Type 1 Diabetes (Mean +/-Standard Deviation)

Figure 4: Change from Baseline FEV1 (L) in Patients with Type 2 Diabetes (Mean +/- Standard Deviation)

Following 2 years of EXUBERA treatment in patients with type 1 and type 2 diabetes, the difference between treatment groups for the mean change from baseline FEV1 was approximately 40 mL, favoring the comparator.

Figure 5: Change from Baseline DLco (mL/min/mmHg) in Patients with Type 1 Diabetes (Mean +/- Standard Deviation)

Figure 6: Change from Baseline DLco (mL/min/mmHg) in Patients with Type 2 Diabetes (Mean +/- Standard Deviation)

Following 2 years of EXUBERA treatment, the difference between treatment groups for the mean change from baseline DLCO was approximately 0.5mL/min/mmHg (type 1 diabetes), favoring the comparator, and approximately 0.1mL/min/mmHg (type 2 diabetes), favoring EXUBERA.

During the two-year clinical trials, individual patients experienced notable declines in pulmonary function in both treatment groups. A decline from baseline FEV1 of ≥ 20% at last observation occurred in 1.5% of EXUBERA-treated and 1.3% of comparator-treated patients. A decline from baseline DLCO of ≥ 20% at last observation occurred in 5.1% of EXUBERA-treated and 3.6% of comparator treated patients.

OVERDOSAGE

Hypoglycemia may occur as a result of an excess of insulin relative to food intake, energy expenditure, or both.

Mild to moderate episodes of hypoglycemia usually can be treated with oral glucose. Adjustments in drug dosage, meal patterns, or exercise, may be needed.

Severe episodes of hypoglycemia with coma, seizure, or neurologic impairment may be treated with intramuscular/subcutaneous glucagon or concentrated intravenous glucose. Sustained carbohydrate intake and observation may be necessary because hypoglycemia may recur after apparent clinical recovery.

DOSAGE AND ADMINISTRATION

EXUBERA, like rapid-acting insulin analogs, has a more rapid onset of glucose-lowering activity compared to subcutaneously injected regular human insulin. EXUBERA has a duration of glucose-lowering activity comparable to subcutaneously injected regular human insulin and longer than rapid-acting insulin. EXUBERA doses should be administered immediately prior to meals (no more than 10 minutes prior to each meal).

In patients with type 1 diabetes, EXUBERA should be used in regimens that include a longer-acting insulin. For patients with type 2 diabetes, EXUBERA may be used as monotherapy or in combination with oral agents or longer-acting insulin.

Because of the effect of EXUBERA on pulmonary function, all patients should have pulmonary function assessed prior to initiating therapy with EXUBERA. Periodic monitoring of pulmonary function is recommended for patients being treated with EXUBERA (see PRECAUTIONS, Pulmonary Function).

EXUBERA is intended for administration by inhalation and must only be administered using the EXUBERA® Inhaler. Refer to the EXUBERA Medication Guide for a description of the EXUBERA® Inhaler and for instructions on how to use the inhaler.

Calculation of Initial Pre-Meal EXUBERA Dose

The initial dosage of EXUBERA should be individualized and determined based on the physician's advice in accordance with the needs of the patient. Recommended initial pre-meal doses are based on clinical trials in which patients were requested to eat three meals per day. Initial pre-meal doses may be calculated using the following formula: [Body weight (kg) X 0.05 mg/kg = pre-meal dose (mg)] rounded down to the nearest whole milligram number (e.g., 3.7 mg rounded down to 3 mg).

Approximate guidelines for initial, pre-meal EXUBERA doses, based on patient body weight, are indicated in Table 7:

Table 7: Approximate Guidelines for Initial, Pre-Meal EXUBERA Dose (based on patient body weight)
Patient Weight (in kg) | Patient Weight (in lb) | Initial Dose per Meal | Number of 1 mg Blisters per Dose | Number of 3 mg Blisters per Dose
30 to 39.9 kg | 66 – 87 lb | 1 mg per meal | 1 | -
40 to 59.9 kg | 88 – 132 lb | 2 mg per meal | 2 | -
60 to 79.9 kg | 133 – 176 lb | 3 mg per meal | - | 1
80 to 99.9 kg | 177 – 220 lb | 4 mg per meal | 1 | 1
100 to 119.9 kg | 221– 264 lb | 5 mg per meal | 2 | 1
120 to 139.9 kg | 265 – 308 lb | 6 mg per meal | - | 2

A 1 mg blister of EXUBERA inhaled insulin is approximately equivalent to 3 IU of subcutaneously injected regular human insulin. A 3 mg blister of EXUBERA inhaled insulin is approximately equivalent to 8 IU of subcutaneously injected regular human insulin. Table 8 provides the approximate IU dose of regular subcutaneous human insulin for EXUBERA inhaled insulin doses from 1 mg to 6 mg.

Table 8: Approximate Equivalent IU Dose of Regular Human Subcutaneous Insulin for EXUBERA Inhaled Insulin Doses Ranging from 1 mg to 6 mg
Dose (mg) | Approximate Regular Insulin SC Dose in IU | Number of 1 mg EXUBERA Blisters per Dose | Number of 3 mg EXUBERA Blisters per Dose
1 mg | 3 | 1 | -
2 mg | 6 | 2 | -
3 mg | 8 | - | 1
4 mg | 11 | 1 | 1
5 mg | 14 | 2 | 1
6 mg | 16 | - | 2

Patients should combine 1 mg and 3 mg blisters so that the least number of blisters per dose are taken (e.g., a 4 mg dose should be administered as one 1 mg blister and one 3 mg blister). Consecutive inhalation of three 1 mg unit dose blisters results in significantly greater insulin exposure than inhalation of one 3 mg unit dose blister. Therefore, three 1 mg doses should not be substituted for one 3 mg dose (see CLINICAL PHARMACOLOGY, Pharmacokinetics). When a patient is stabilized on a dosing regimen that includes 3 mg blisters, and the 3 mg blisters become temporarily unavailable, the patient can temporarily substitute two 1 mg blisters for one 3 mg blister. Blood glucose should be monitored closely.

As with all insulins, additional factors that should be taken into consideration when determining the EXUBERA starting dose include, but are not limited to, patient's current glycemic control, previous response to insulin, duration of diabetes, and dietary and exercise habits.

Considerations for Dose Titration

After initiating EXUBERA therapy, as with other glucose-lowering agents, dose adjustment may be required based on the patient's need (e.g., blood glucose concentrations, meal size and nutrient composition, time of day and recent or anticipated exercise). Each patient should be titrated to their optimal dosage based on blood glucose monitoring results.

As for all insulins, the time course of EXUBERA action may vary in different individuals or at different times in the same individual.

EXUBERA may be used during intercurrent respiratory illness (e.g., bronchitis, upper respiratory tract infection, rhinitis). Close monitoring of blood glucose concentrations and dose adjustment may be required on an individual basis. Inhaled medicinal products (e.g. bronchodilators) should be administered prior to administration of EXUBERA.

HOW SUPPLIED

EXUBERA (insulin human [rDNA origin]) Inhalation Powder is available in 1 mg and 3 mg unit dose blisters. The blisters are dispensed on perforated cards of six unit dose blisters (PVC/Aluminum). The two strengths are differentiated by color print and tactile marks that can be differentiated by touch. The 1 mg blisters and respective perforated cards are printed with green ink and the cards are marked with one raised bar. The 3 mg blisters and respective perforated cards are printed with blue ink and the cards are marked with three raised bars.

Five blister cards are packaged in a clear plastic (PET) thermoformed tray. Each PET tray also contains a desiccant and is covered with a clear plastic (PET) lid. The tray of five blister cards (30 unit dose blisters) is sealed in a foil laminate pouch with a desiccant.

EXUBERA (insulin human [rDNA origin]) Inhalation Powder blisters, an EXUBERA® Inhaler, and replacement EXUBERA® Release Units are required to initiate therapy with EXUBERA and are provided in the EXUBERA Kit. A fully assembled EXUBERA® Inhaler consists of the inhaler base, a chamber, and an EXUBERA® Release Unit. A fully assembled Inhaler is packaged with a replacement Chamber and is available in the EXUBERA Kit and as a separate unit. The Chamber is also available as an individual component.

EXUBERA® Release Units are individually packaged in a sealed thermoformed tray. One EXUBERA® Release Unit is included in each fully assembled Inhaler. Two additional Release Units are provided in the EXUBERA Kit and in each Combination Pack. EXUBERA Release Units are also available individually.

See Tables 9 and 10 for a description of these configurations.

Table 9
EXUBERA (insulin human [rDNA origin]) Inhalation Powder is available as follows:
Description | Contents | NDC
EXUBERA KIT | 1 EXUBERA Inhaler 1 Replacement Chamber 1 mg × 180 blisters 3 mg × 90 blisters 2 EXUBERA® Release Units | 0069-0050-85
EXUBERA Combination Pack 12 | 1 mg × 90 blisters 3 mg × 90 blisters 2 EXUBERA® Release Units | 0069-0050-19
EXUBERA Combination Pack 15 | 1 mg × 180 blisters 3 mg × 90 blisters 2 EXUBERA® Release Units | 0069-0050-53
EXUBERA 1 mg Patient Pack | 90 × 1 mg 2 EXUBERA® Release Units | 0069-0707-37
EXUBERA 3 mg Patient Pack | 90 × 3 mg 2 EXUBERA® Release Units | 0069-0724-37

Table 10
EXUBERA® Inhaler and Components are available as follows:
Description | Contents | NDC
EXUBERA® Inhaler & Chamber | 1 EXUBERA® Inhaler 1 Replacement Chamber | 0069-0054-19
EXUBERA® Release Units | 2 EXUBERA® Release Units | 0069-0097-41
EXUBERA® Chamber | 1 Replacement Chamber | 0069-0061-19

STORAGE AND HANDLING

Blister Storage

Not in-use (Unopened): Store at controlled room temperature, 25°C (77°F); excursions permitted to 15–30°C (59–86°F) [see USP Controlled Room Temperature]. Do not freeze. Do not refrigerate.

In-use: Once the foil overwrap is opened, unit dose blisters should be protected from moisture, stored at 25°C (77°F); excursions permitted to 15–30°C (59–86°F) [see USP Controlled Room Temperature]. Do not freeze. Do not refrigerate. Unit dose blisters should be used within 3 months after opening the foil overwrap. Return the blisters to the overwrap to protect from moisture. Additional care should be taken to avoid humid environments, e.g. steamy bathroom following a shower.

Discard blister if frozen.

Inhaler Storage

Store at controlled room temperature, 25°C (77°F); excursions permitted to 15–30°C (59–86°F) [see USP Controlled Room Temperature]. Do not freeze. Do not refrigerate.

The EXUBERA® Inhaler can be used for up to 1 year from the date of first use.

Replacing The EXUBERA® Release Unit

The EXUBERA® Release Unit in the EXUBERA® Inhaler should be changed every 2 weeks.

Keep out of reach of children

Rx only

LAB-0331-12.0

April 2008

SPL SUPPLEMENTAL PATIENT MATERIAL

Medication Guide EXUBERA® (eg-ZU-ber-uh) (insulin human [rDNA origin]) Inhalation Powder

Carefully read the Instructions for Use at the end of this Medication Guide, so you will be sure to get the right amount of your insulin.

Read this Medication Guide that comes with EXUBERA before you start using it, and each time you get a refill. There may be new information. This Medication Guide does not take the place of talking with your healthcare provider about your medical condition or treatment.

What is the most important information I should know about EXUBERA?

- EXUBERA is a prescription medicine that contains an insulin powder that you breathe in (inhale) through your mouth using the EXUBERA® Inhaler. It is used to treat adults with diabetes. It helps to control high blood sugar.
- Do not use EXUBERA if you smoke, start smoking, or if you quit smoking less than 6 months ago. Smoking can increase the amount of EXUBERA you get and may cause your blood sugar to get dangerously low. If you smoke, or you quit smoking less than 6 months ago, you will need a different treatment for your diabetes.
- EXUBERA may lower your lung function, so:
  - You need to have lung tests before you start EXUBERA, and after you start EXUBERA, you may need to have lung tests again later as directed by your healthcare provider.
  - EXUBERA is not recommended for people that have chronic lung disease (such as asthma or chronic obstructive pulmonary disease or emphysema).
  - Also, EXUBERA should not be used at all by people with unstable or poorly controlled lung disease.
- The dose of EXUBERA is different from other insulin. Make sure you take the exact dose of EXUBERA that your healthcare provider prescribes.
- EXUBERA comes in 1 mg dose or in 3 mg dose "blisters", which are small foil dose packets. "Blister" is a standard term for the shape and type of foil dose packet that holds the insulin powder. Each individual dose of EXUBERA is enclosed in one of these small foil "blister" packets. For the rest of this Medication Guide, these small foil "blister" dose packets will just be called blisters. These blisters come packaged together in a larger foil overwrap package.
- Make sure you get the right dose from your pharmacy. Do not use three 1 mg blisters in place of one 3 mg blister because you may get too much insulin. If you use 3 mg blisters as a part of your usual dosing and you cannot get the 3 mg blisters for some time, call your healthcare provider for advice. If you need to take the insulin before you have spoken to your healthcare provider, use two 1 mg blisters as a temporary replacement for one 3 mg blister. Then, check your blood sugar levels and continue to call your healthcare provider for advice.

What is EXUBERA?

- EXUBERA is a prescription medicine that contains an insulin powder that you breathe in (inhale) through your mouth using the EXUBERA® Inhaler. It is used to treat adults with diabetes. It helps to control high blood sugar.
- For adults with type 2 diabetes, EXUBERA may be used by itself, or with diabetes pills, or with a longer-acting insulin.
- For adults with type 1 diabetes, EXUBERA is always used with treatment that includes a longer-acting insulin.
- EXUBERA contains a short- or rapid-acting form of insulin. It should NOT be taken at the same time as other short- or rapid-acting insulins. It is not a longer-acting insulin.
- EXUBERA inhaled insulin starts working faster than regular injected insulin. It works as long as regular injected insulin. When used as your mealtime insulin, EXUBERA should be used within 10 minutes before your meal.
- The insulin in EXUBERA is a man-made insulin that is the same as the insulin made by the human body.

What is Diabetes?

- Diabetes is a disease that affects the amount of insulin and sugar in your body. Your body needs insulin to turn sugar (glucose) into energy. With diabetes, your body may not make enough insulin. If this is the case, you need to take more insulin. Taking insulin will help to keep you from having too much sugar in your blood.
- Treatment with insulin helps to keep your diabetes under control. The way you live helps, as well. Watch your diet. Check your blood sugar levels. Exercise. Plan to be active. These good habits work with your insulin to help you control your diabetes.
- Ask your healthcare provider for more information about diabetes.

Who should NOT use EXUBERA?

Do not use EXUBERA if you:

- smoke or stopped smoking less than 6 months ago. If you start smoking or resume smoking, stop using EXUBERA right away. See your healthcare provider right away for a different treatment.
- have an unstable or poorly controlled lung disease (such as unstable or poorly controlled asthma, chronic obstructive pulmonary disease or emphysema).
- are allergic to insulin or any of the inactive ingredients in EXUBERA. See the end of this leaflet for a list of ingredients in EXUBERA.

Children and teenagers should not use EXUBERA, because it has not been tested enough in children and teenagers under 18 years of age.

What should I tell my healthcare provider before starting EXUBERA?

Tell your healthcare provider about all your health and medical conditions, including if you:

- have any lung disease or have breathing problems.
- are using any inhaled medications
- have liver or kidney problems. Your dose may need to be adjusted.
- are pregnant or plan to become pregnant. EXUBERA has not been tested enough in pregnant females. It is very important to maintain control of your blood sugar levels during pregnancy. Your healthcare provider will decide which insulin is best for you during your pregnancy.
- are breast-feeding or plan to breast-feed. Many medicines, including insulin, pass into breast milk, and could affect your baby. Talk to your healthcare provider about the best way to feed your baby.
- are smoking or have recently stopped smoking.
- are taking any medicines or supplements. This includes: 1) medicines you get with a prescription, 2) those you get without a prescription and 3) herbal supplements and vitamins. Ask your healthcare provider for advice if you take other medicines. See "What can affect how much insulin I need?".

How should I take EXUBERA?

See the end of this Medication Guide for the Instructions for Use for using EXUBERA blisters with the EXUBERA® Inhaler. Make sure your healthcare provider teaches you the right way to use EXUBERA blisters with the EXUBERA® Inhaler and make sure you understand everything.

- Follow the medicine instructions that your healthcare provider gives you. Do not make any changes with your insulin unless you have talked to your healthcare provider. Your insulin needs may change because of 1) illness 2) stress, 3) other medicines or 4) changes in diet or activity level. Talk to your healthcare provider about how to adjust your insulin dose.
- Do not change any of your other diabetes medicines without talking to your healthcare provider. This includes insulin that you now inject. It also includes any diabetes medicines you may now take by mouth. Your healthcare provider may need to adjust the doses of your other diabetes medicines.
- Follow your healthcare provider's instructions for testing your blood sugar. Ask what to do if it is high or low. Low blood sugar (hypoglycemia) is the most common side effect of EXUBERA and all insulin.
- Never use three 1 mg blisters for one 3 mg blister because you may get too much insulin. If your 3 mg blisters become temporarily unavailable, use only two 1 mg blisters instead and check your blood sugar levels. Call your healthcare provider to get a new supply of 3 mg blisters as soon as possible. See "What is the most important information I should know about EXUBERA?"
- Do not open the individual EXUBERA blisters. The EXUBERA® Inhaler is designed to open the blister after you put the unopened blister in the Inhaler. You don't need to open the blister yourself.
- Never swallow the contents of the EXUBERA blister. You should only breathe in EXUBERA using the EXUBERA® Inhaler. Do not try to breathe in the EXUBERA insulin powder without using the EXUBERA® Inhaler.
- After a blister has been used, throw it away. Do not try to re-use a blister.
- You should take EXUBERA within 10 minutes before a meal.
- You need to have lung tests before you start EXUBERA, and after you start EXUBERA, you may need to have lung tests again as directed by your healthcare provider.
- If you are having problems with your EXUBERA® Inhaler or it breaks and you need a replacement, call 1-800-EXUBERA. Then, call your healthcare provider for treatment instructions until you receive your replacement Inhaler.

What can affect how much insulin I need?

Talk to your healthcare provider if you have any questions about how much insulin you need. Many things can affect how much insulin you need, including:

- Illness: Illness may change how much insulin you need. It is a good idea to think ahead and make a "sick day" plan with your healthcare provider. Do this in advance, so you will be ready when this happens. Be sure to test your blood sugar more often. Be sure to call your healthcare provider if you are sick.
- Medicines: Many medicines can affect your insulin needs. Other medicines can change the way insulin works. This includes prescription and non-prescription medicines, vitamins, and herbal supplements. You may need a different dose of insulin when you are taking certain other medicines. Know all the medicines you take. Keep a list. Show this list to all your healthcare providers and pharmacists anytime you get a new medicine or refill. Your healthcare provider will tell you if your insulin dose needs to be changed.
- Meals. The amount of food you eat can affect your insulin needs. You may need a different dose of insulin if you: 1) eat less food 2) skip meals, or 3) eat more food than usual. Talk to your healthcare provider if you change your diet. This will help you know how to adjust your EXUBERA and other insulin doses.
- Alcohol. Alcohol may affect the way your insulin works and affect your blood sugar levels. Beer and wine, as well as other kinds of alcohol, can cause these problems with your blood sugar levels. Talk to your healthcare provider about drinking alcohol.
- Exercise or Activity Level. Exercise or activity level may change the way your body uses insulin. Check with your healthcare provider before you start an exercise program. Do this, because your dose may need to be changed.
- Travel. If you are going to travel across time zones, talk with your healthcare provider about how to time your dosing. When you travel, wear your medical alert identification. Take extra insulin and supplies with you.

What are some of the possible side effects of EXUBERA?

1. Low blood sugar (HYPOglycemia):

As with all forms of insulin, a possible side effect of EXUBERA is low blood sugar. Low blood sugar is often called "hypoglycemia" or an "insulin reaction". It may happen when you do not have enough sugar in your blood. Common causes of low blood sugar are: 1) illness, 2) emotional or physical stress, 3) too much insulin, 4) too little food or missed meals, and 5) too much exercise or activity.

Early warning signs of low blood sugar may differ from person to person. For some people, signs may be easy to notice. For others, signs may be harder to notice, if noticed at all. That is why it is important to check your blood sugar as your healthcare provider has advised you.

Low blood sugar can happen with:

- The wrong insulin dose. This can happen when you take too much insulin.
- Not enough food intake. This can happen if a meal or snack is missed or delayed.
- Vomiting or diarrhea that decreases the amount of sugar absorbed by your body.
- Drinking alcohol.
- Medicines that affect insulin. Be sure to discuss all your medicines with your healthcare provider. Do not start any new medicines until you know how they may affect your insulin dose.
- Medical conditions that can affect your blood sugar levels or insulin. These conditions include diseases of: 1) the adrenal glands, 2) the pituitary, 3) the thyroid gland, 4) the liver, and 5) the kidneys.
- Too much blood sugar use by the body. This can happen if you exercise too much or have a fever.

Low blood sugar can be mild to severe. It can start quickly.

The following patients may have few or no warning symptoms of hypoglycemia:

- patients who have had diabetes for a long time
- patients with diabetic nerve problems (neuropathy) - for example, numbness in the feet
- patients using certain medicines for high blood pressure or heart problems.

Symptoms of low blood sugar may include:

- shaking (tremor)
- sweating
- anxiety, irritability, restlessness, trouble concentrating, personality changes, mood changes, or other abnormal behavior
- tingling in your hands, feet, lips, or tongue
- dizziness, light-headedness, or drowsiness
- nightmares or trouble sleeping
- headache
- blurred vision
- slurred speech
- fast heart beat (palpitations)
- unsteady walking (unsteady gait)

Low blood sugar is a problem:

- Driving and using machinery: If you have low blood sugar, your ability to concentrate or react may be reduced so that you may be less able to drive a vehicle or use mechanical equipment. If you do, you may risk causing injury to yourself or others.
- Effects on your heart and brain: Severe low blood sugar can be dangerous. It can cause temporary or permanent harm to your heart or brain. It may even cause unconsciousness, seizures, or death.

What to do about low blood sugar:

- Juice or food can treat low blood sugar. Mild to moderate low blood sugar can be treated by eating or drinking carbohydrates such as fruit juice, raisins, sugar candies, milk, or glucose tablets. Talk to your healthcare provider about the amount of carbohydrates you should eat to treat mild to moderate low blood sugar.
- Talk to your healthcare provider if : 1) you have low blood sugar often, or 2) it is hard for you to know if you have the symptoms of low blood sugar.
- Getting emergency help: Plan for a way to get medical help if you need it. Severe low blood sugar may require the help of another person or emergency medical personnel. A person with low blood sugar who cannot take foods or liquids with sugar by mouth will need medical help fast and treatment with: 1) a glucagon injection or 2) glucose given intravenously (IV). Without medical help right away, serious reactions or even death could occur.

2. High Blood Sugar (HYPERglycemia):

High blood sugar may occur when you have diabetes, even while you are on insulin treatment. High blood sugar is often called "hyperglycemia". It may occur when you have too much sugar in your blood. Usually, it means there is not enough insulin to break down the food you eat into energy your body can use.

High blood sugar can happen with:

- The wrong insulin dose. This can happen from:
  - taking too little or no insulin
  - incorrect storage of insulin (freezing, or too much heat)
  - using insulin after the expiration date.
- Too much carbohydrate intake (includes starchy foods, fruits and sweet foods and drinks). This can happen if you 1) eat larger meals, 2) eat more often, or 3) increase the amount of carbohydrate in your meals.
- Medicines that affect insulin. Be sure to discuss all your medicines with your healthcare provider. Do not start any new medicines until you know how they may affect your insulin dose.
- Medical conditions that affect insulin. These medical conditions include 1) fevers, 2) infections, 3) heart attacks, and 4) stress.

High blood sugar can be a serious problem.

- High blood sugar can be mild or severe.
- When your blood sugar is extremely high, it can cause very serious problems that need treatment right away.
- These severe states can result in unconsciousness and death.

What are the symptoms of high blood sugar?

Often, high blood sugar has no symptoms at all. When high blood sugar does have symptoms, they can include:

- confusion or drowsiness
- increased thirst
- decreased appetite, nausea, or vomiting
- rapid heart rate
- increased urination and dehydration (too little fluid in your body)
- fruity smelling breath
- fast, deep breathing
- pain in the stomach area (abdominal pain)

Test your blood sugar levels to prevent problems.

- Because some patients get few symptoms of high blood sugar, it is important to check your blood sugar regularly.
- Testing your blood often for your blood sugar level will let you know if you have high blood sugar.
- If your tests are often high, tell your healthcare provider as soon as possible so your dose of medicine can be changed.
- Talk to your healthcare provider to find out what blood sugar level is too high for you. Ask about when you should call your healthcare provider for a high blood sugar level. Also ask about what blood sugar number is high enough that you should go straight to the hospital.

3. Effect on Lung Function:

EXUBERA may lower your lung function. See "What is the most important information I should know about EXUBERA?"

- You need to have lung tests before you start EXUBERA, and after you start EXUBERA, you may need to have lung tests again later as directed by your healthcare provider.
- If you notice a change in your breathing while taking EXUBERA, call your healthcare provider.

4. Serious allergic reactions:

Sometimes severe, life-threatening allergic reactions can happen with insulin. If you think you are having a severe allergic reaction, get medical help right away. Signs of insulin allergy include:

- a rash all over your body
- shortness of breath
- wheezing (trouble breathing)
- a fast pulse
- sweating
- low blood pressure

5. EXUBERA may cause a cough, dry mouth, or chest discomfort.

Tell your healthcare provider if you have any side effects that bother you.

These are not all the side effects that can happen with EXUBERA. Ask your healthcare provider or pharmacist for more information.

6. In studies of EXUBERA in people with diabetes, lung cancer occurred in a few more people who were taking EXUBERA than in people who were taking other diabetes medicines. All the people in these studies who developed lung cancer used to smoke cigarettes. There were too few cases to know if the lung cancer was related to EXUBERA.

How should I store EXUBERA?

- Store EXUBERA in a dry place at room temperature below 86° F (the same as below 30° C). Be sure to protect the small foil blisters from humid places, from steam and from water.
- Do not refrigerate or freeze EXUBERA, or expose it to excessive heat. If an EXUBERA blister freezes or is exposed to excessive heat, throw it away.

Keep EXUBERA and all medicines out of the reach of children.

General Information about EXUBERA

- Medicines are sometimes prescribed for purposes other than those listed in a Medication Guide. Do not use EXUBERA for a condition for which it was not prescribed.
- Do not give or share EXUBERA with another person, even if they have diabetes also. It may harm them.

For more information about EXUBERA:

- Talk with your healthcare provider. This Medication Guide only summarizes the most important information about EXUBERA.
- You can also ask your healthcare provider or pharmacist for information about EXUBERA that is written for healthcare professionals.
- Call 1-800-EXUBERA or go to website www.exubera.com.

What are the ingredients of EXUBERA?

Active ingredient: human insulin

Inactive ingredients: sodium citrate (dihydrate), mannitol, glycine, and sodium hydroxide

Instructions for Use

Please read these instructions carefully before starting to use your EXUBERA® Inhaler. Keep this Medication Guide, as you may need to read it again. Make sure you understand everything. Talk to your healthcare provider if you do not understand the instructions. Always be sure you have the correct EXUBERA blisters available before using your EXUBERA® Inhaler. EXUBERA blisters must only be used with the EXUBERA® Inhaler.

KNOW THE PARTS OF YOUR EXUBERA® INHALER

HOW TO TAKE YOUR DOSE

Step 1: Set up your EXUBERA® Inhaler

Hold your EXUBERA® Inhaler in your hand. Be sure that the words "EXUBERA® Inhaler" at the top face you.

Hold the black ring at the bottom of the base and use it to pull the base out of the chamber.

You will hear a click when the EXUBERA® Inhaler is fully extended and locked into place. The bottom of the chamber MUST be above the gray button.

Step 2: Load your EXUBERA blister

Hold the EXUBERA blister by the tab with printed side up and with the notch pointed towards the EXUBERA® Inhaler and insert one blister into the slot. Do not open the EXUBERA blister.

Slide one EXUBERA blister straight into the slot as far as it will go.

Step 3: Getting ready to take your dose

Make sure that the mouthpiece is closed. If the mouthpiece is open, turn it around so that it is closed.

Pull out the blue handle from the bottom as far as it will go.

Squeeze the handle until it snaps shut. This will put pressure in the system.

Stand or sit up straight.

Step 4: Inhale your insulin dose

Perform the following steps in order.

Hold the EXUBERA® Inhaler upright with the blue button facing towards you. Push the blue button until it clicks and watch for the insulin cloud to fill the chamber. If a cloud does not appear right away, press the gray button, pull out the used EXUBERA blister, go back to Step 2 and repeat. If the blister is punctured or appears damaged, use a new blister.

Breathe out normally.

After the cloud appears, right away turn the mouthpiece around. The mouthpiece should now be facing towards you.

Promptly place the mouthpiece fully in the mouth, forming a seal around the mouthpiece with your lips, so that the insulin will not leak out.

Do not block the opening of the mouthpiece with your tongue or teeth. Do not blow into the mouthpiece.

In one breath, slowly and deeply breathe the insulin cloud in through your mouth.

Take the mouthpiece out of your mouth.

Close your mouth and hold your breath for 5 seconds.

Breathe out normally.

Step 5: After your dose

Turn the mouthpiece back to its closed position.

Press the gray button and pull out the used EXUBERA blister.

If you need another blister as part of your dose, repeat steps 2, 3 and 4. The contents of only one blister should be inhaled at a time.

Step 6. After your dosing is completed

Squeeze the two chamber release buttons on the side of the base at the same time. Push the base back into the chamber to store the EXUBERA® Inhaler.
Do not store in the refrigerator or freezer.

After a blister has been used, throw it away. Do not try to re-use a blister.

HOW TO TAKE CARE OF YOUR EXUBERA® INHALER

It is important to follow these steps so that your EXUBERA® Inhaler stays clean and works properly.

How to Take your EXUBERA® Inhaler apart

You need to know how to take your EXUBERA® Inhaler apart for you when you need to clean your EXUBERA® Inhaler (once a week), and for when you need to change the EXUBERA® Release Unit (every two weeks). Spare EXUBERA® Release Units should be kept out of children's reach.

Hold the EXUBERA® Inhaler in your hand. Be sure that the words "EXUBERA® Inhaler" at the top face you.

Hold the black ring at the bottom of the base and use it to pull the base out of the chamber.

You will hear a click when the EXUBERA® Inhaler is fully extended and locked into place. The bottom of the chamber MUST be above the gray button.

With one hand, squeeze the two chamber release buttons on the side of the base at the same time while pulling the base all the way out of the chamber with the other hand.

Cleaning

Chamber and mouthpiece – once a week for best functioning. Keeping the chamber and mouthpiece clean is very important to prevent medicine build-up. It is suggested that you choose one day of the week (such as Monday) and clean the chamber and mouthpiece after your last dose for that day every week.

How?

Take your EXUBERA® Inhaler apart.

(See above)

Turn the mouthpiece to the open position.

Dampen a clean soft cloth and use mild liquid soap to wipe the outside and inside of the chamber and mouthpiece.

Do NOT put the chamber in the dishwasher.

Thoroughly rinse the soap out of the chamber and mouthpiece with warm water.

Allow to completely air dry. This will probably take about 4 hours. Make sure that the chamber and mouthpiece are completely dry and that no water droplets remain. Close the mouthpiece. Reattach the chamber to the base.

For instructions on how to attach the chamber to the base, refer to the section "Put your EXUBERA® Inhaler together".

If the washed chamber is not completely dry prior to taking your next dose, use your spare chamber.

Base – clean once a week

How?

Do not put the base in water.

Do not get the inside of the EXUBERA® Release Unit wet. Do not wipe the Release Unit.

Do not use soap or any other cleanser.

Dampen a clean soft cloth with water; do not use a paper towel.

Hold the base upside down with the Release Unit facing the ground. While cleaning the top of the base be careful not to get any water into the Release Unit. Do not take the Release Unit out at this time. Keep the blue handle closed.

Make sure that no water droplets remain.

Wipe only the TOP and OUTSIDE surfaces of the base. Do not wipe the slot where the blister is inserted.

Put your EXUBERA® Inhaler together

Line the top of the base with the open end of the chamber. The blue dot on the bottom of the chamber must be on the same side as the blue button on the base.

Squeeze the two chamber release buttons on the side of the base at the same time. Push the base back into the chamber to store.

Store your EXUBERA® Inhaler in a dry place at room temperature.

Replacing your EXUBERA® Release Unit

Change the Release Unit

Every 2 weeks. You should mark your calendar to remind you when you need to replace the Release Unit. You may also mark the EXUBERA® Release Unit carton in the spaces provided. Be careful when handling the Release Unit, because it has sharp edges. You should not clean the Release Unit.

How?

Take out the used EXUBERA® Release Unit

While the chamber is removed from the base (see "How to take your EXUBERA® Inhaler apart"), hold the base in your hand with the gray button facing you. Turn the used Release Unit about a one-quarter turn counter–clockwise towards the unlock symbol.

Pull the used Release Unit up and out of the base and discard.

Put in a New EXUBERA® Release Unit

Remove the Release Unit from its packaging.

Hold the new Release Unit so the top is facing you. You will see a blue line on it. While holding the Release Unit with one hand, turn the top counter-clockwise with the other hand as far as it will go.

Line up the blue line on the top of the Release Unit with the unlock symbol on the top of the base.

Insert the Release Unit gently into the base. Do not force - it should easily drop into place. (If the new Release Unit does not drop into place or fits tightly, remove and try again). If after several attempts you are not able to insert the Release Unit, try another Release Unit. If you are still having problems, please call 1-800-EXUBERA.

Turn the top of the Release Unit clockwise until the blue line points to the lock symbol on the top of the base. The new Release Unit is now locked in place.

Replacing your EXUBERA® Inhaler and the EXUBERA® Release Unit

You should change your EXUBERA® Inhaler once a year from the date you first use the Inhaler. You can mark the date of first use on the bottom of the Inhaler base.

You should change the EXUBERA® Release Unit in your EXUBERA® Inhaler every 2 weeks. The replacement dates can be marked on the EXUBERA® Release Unit carton.

This Medication Guide has been approved by the U.S. Food and Drug Administration.

EXUBERA is a registered trademark of Pfizer Inc.

Licensed from Nektar

LAB-0333-3.0

April 2008